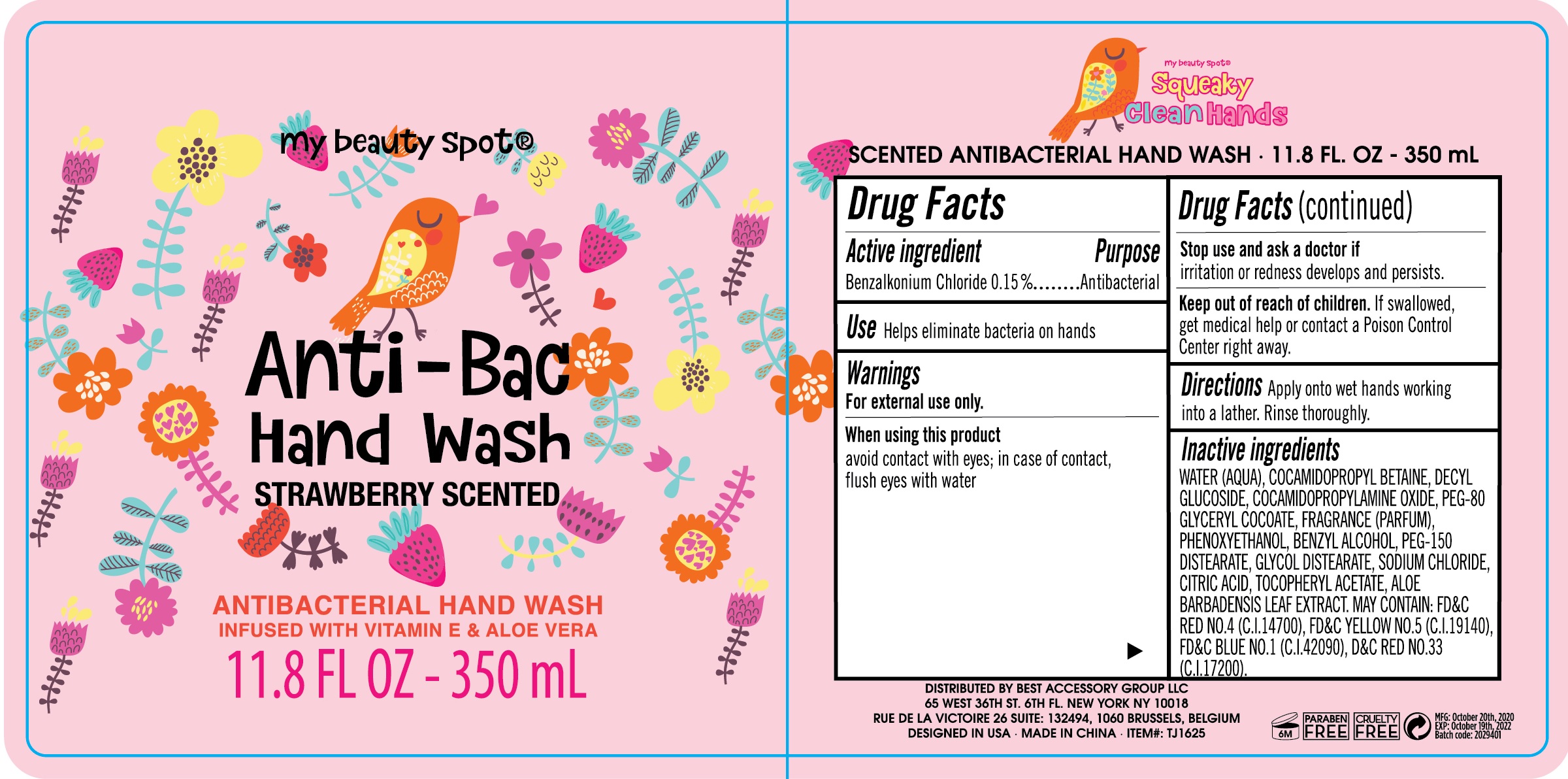 DRUG LABEL: Anti-Bac Hand Wash Strawberry Scented
NDC: 56136-514 | Form: LIQUID
Manufacturer: Ganzhou Olivee Cosmetic Co., Ltd.
Category: otc | Type: HUMAN OTC DRUG LABEL
Date: 20201127

ACTIVE INGREDIENTS: BENZALKONIUM CHLORIDE 1.5 mg/1 mL
INACTIVE INGREDIENTS: WATER; COCAMIDOPROPYL BETAINE; COCAMIDOPROPYLAMINE OXIDE; BENZYL ALCOHOL; GLYCERIN; ACETYLTRIETHYL CITRATE; ASCORBIC ACID; PHENOXYETHANOL; GLYCOL DISTEARATE; SODIUM CHLORIDE; .ALPHA.-TOCOPHEROL ACETATE, D-; ALOE VERA LEAF

Hand Wash

Active ingredient

Benzalkonium Chloride 0.1500%

Purpose

Antibacterial

USE

Helps eliminate bacteria on hands

warnings:

For external use only.

When using this product, avoid contact with eyes; in case of contact, flush eyes with water

Stop use and ask a doctor if irritation or redness develops and persists.

KEEP OUT OF REACH OF CHILDREN

If swallowed, get medical help or contact a Poison Control Center right away.

Directions

Apply onto wet hands working into a lather. Rinse thorougly.

Inactive ingredients

Water (Aqua), Cocamidopropyl Betaine, Decyl Glucoside, Cocamidopropylamine Oxide Peg-80 Glyceryl Cocoate, Fragrance (Parfum), Phenoxyethanol, Benzyl Alcohol, Peg-15 Distearate, Glycol Distearate, Sodium Chloride, Citric Acid, Tocopheryl Acetat, Aloe Barbadnsis Leaf Extract. May contain: FD &C Red No. 4 (C.I. 14700), FD&C Yellow No. 5 (C.I. 19140), FD&C Blue No. 1 (C.I. 42090), FD&C Red No.33 (C.I. 17200).